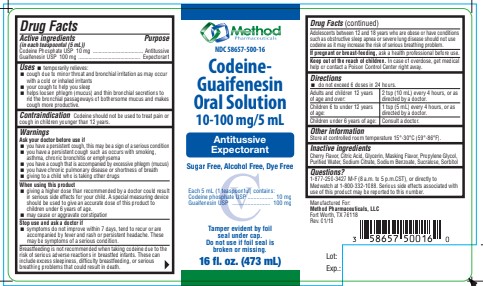 DRUG LABEL: Codeine-Guaifenesin
NDC: 58657-500 | Form: SOLUTION
Manufacturer: Method Pharmaceuticals, LLC
Category: otc | Type: HUMAN OTC DRUG LABEL
Date: 20251021
DEA Schedule: CIII

ACTIVE INGREDIENTS: CODEINE PHOSPHATE 10 mg/5 mL; GUAIFENESIN 100 mg/5 mL
INACTIVE INGREDIENTS: CITRIC ACID MONOHYDRATE; GLYCERIN; PROPYLENE GLYCOL; WATER; SODIUM CITRATE; SUCRALOSE; SORBITOL; SODIUM BENZOATE

Codeine-Guaifenesin Oral Solution

Active ingredient

(in each teaspoonful (5 mL))
Codeine Phosphate USP 10 mg

Purpose

Antitussive

Active ingredient

(in each teaspoonful (5 mL))
Guaifenesin USP 100 mg

Purpose

Expectorant

Uses

- temporarily relieves:
- cough due to minor throat and bronchial irritation as may occur with a cold or inhaled irritants
- your cough to help you sleep
- helps loosen phlegm (mucus) and thin bronchial secretions to rid the bronchial passageways of bothersome mucus and makes cough more productive.

Warnings

Ask your doctor before use if

- you have a persistent cough, this may be a sign of a serious condition
- you have a persistent cough such as occurs with smoking, asthma, chronic bronchitis or emphysema
- you have a cough that is accompanied by excessive phlegm (mucus)
- you have chronic pulmonary disease or shortness of breath
- giving to a child who is taking other drugs

When using this product

- giving a higher dose than recommended by a doctor could result in serious side effects for your child. A special measuring device should be used to give an accurate dose of this product to children under 6 years of age.
- may cause or aggravate constipation

Stop use and ask a doctor if

- symptoms do not improve within 7 days, tend to recur or are accompanied by fever and rash or persistent headache. These may be symptoms of a serious condition.

If pregnant or breast-feeding

ask a health professional before use.

Keep out of reach of children.

In case of overdose, get medical help or contact a Poison Control Center right away.

Directions

- do not exceed 6 doses in 24 hours.

Adults and children 12 years of age and over: | 2 tsp (10 mL) every 4 hours, or as directed by a doctor.
Children 6 to under 12 years of age: | 1 tsp (5 mL) every 4 hours, or as directed by a doctor.
Children under 6 years of age: | Consult a doctor.

Other information

Store at controlled room temperature 15°-30°C (59°-86°F).

Inactive ingredients

Cherry Flavor, Citric Acid, Glycerin,Masking flavor, Propylene glycol, Purified Water, Sodium Citrate, Sodium Benzoate, Sucralose Sorbitol.

Principal Display Panel

NDC 58657-500-16
Codeine-Guaifenesin Oral Solution
10-100 mg/5 mL
Antitussive
Expectorant
16 fl. oz. (473 mL)